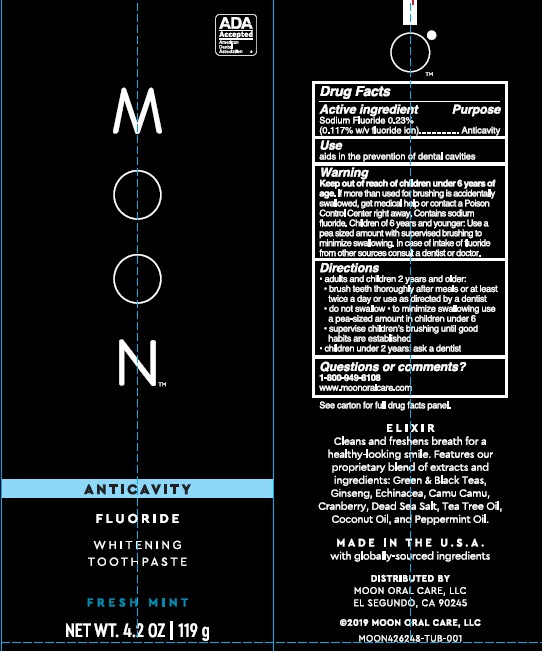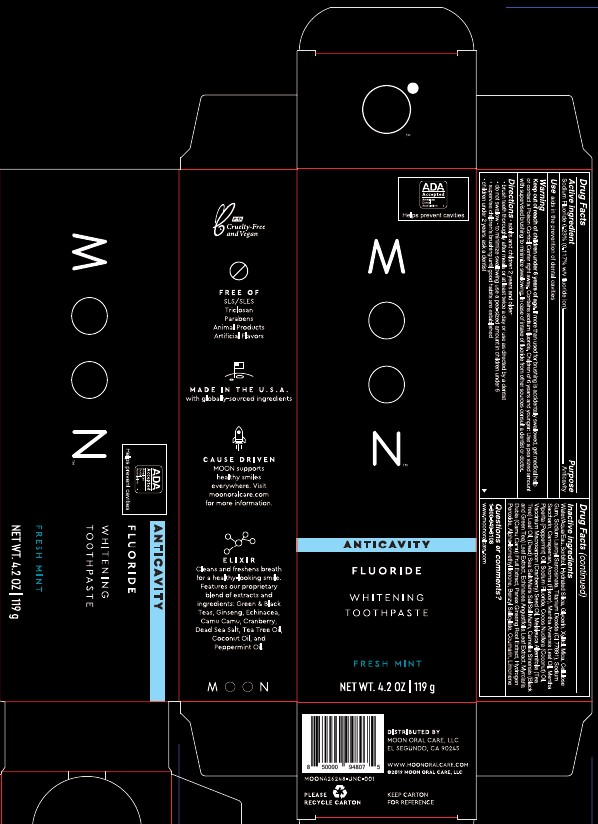 DRUG LABEL: Moon Whitening Anticavity
NDC: 82214-002 | Form: PASTE
Manufacturer: Moon Oral Care, LLC
Category: otc | Type: HUMAN OTC DRUG LABEL
Date: 20260109

ACTIVE INGREDIENTS: SODIUM FLUORIDE 0.23 g/100 g
INACTIVE INGREDIENTS: HYDRATED SILICA; MICA; WATER; SEA SALT; PEPPERMINT OIL; TEA TREE OIL; ASIAN GINSENG; SORBITOL; GLYCERIN; MYRCIARIA DUBIA FRUIT; HYDROGEN PEROXIDE; COCONUT OIL; CARBOXYMETHYLCELLULOSE SODIUM, UNSPECIFIED; GREEN TEA LEAF; SACCHARIN SODIUM; ECHINACEA ANGUSTIFOLIA LEAF; XYLITOL; SODIUM LAUROYL SARCOSINATE; TITANIUM DIOXIDE; CARRAGEENAN; MENTHA ARVENSIS LEAF OIL; CRANBERRY SEED OIL; ALPHA-ISOMETHYL IONONE; BENZYL SALICYLATE; LIMONENE, (+)-; COUMARIN

ACTIVE INGREDIENT

Sodium Fluoride 0.23% (0.117% w/v fluoride ion) Anticavity

PURPOSE

Anticavity

DOSAGE AND ADMINISTRATION

Topical Paste

INDICATIONS AND USAGE

Aids in the prevention of dental cavities.

Warning:

Keep out of reach of children under 6 years of age. If more than used for brushing is accidentally swallowed, get medical help or contact a Poison Control Center right away. Contains sodium fluoride. Children of 6 years and younger: Use a pea-sized amount with supervised brushing to minimize swallowing. In case of intake of fluoride from other sources consult a dentist or doctor.

INSTRUCTIONS FOR USE

Directions: Adults and children 2 years and older: Brush teeth thoroughly after meals at least twice a day or use as directed by a dentist. Do not swallow. To minimize swallowing, use a pea-sized amount in children under 6. Supervise children's brushing until good habits are established. Children under 2 years ask a dentist

Keep out of reach of children under 6 years of age. If more than used for brushing is accidentally swallowed, get medical help or contact a Poison Control Center right away.

INACTIVE INGREDIENT

WATER, SORBITOL, HYDRATED SILICA, GLYCERIN, XYLITOL, MICA, CELLULOSE GUM, SODIUM LAUROYL SARCOSINATE, TITANIUM DIOXIDE, SACCHARIN SODIUM, CARRAGEENAN, FLAVOR, MENTHA ARVENSIS LEAF OIL, PEPPERMINT OIL, COCONUT OIL, CRANBERRY SEED OIL, TEA TREE OIL, SEA SALT, GREEN TEA LEAF, ECHINACEA ANGUSTIFOLIA LEAF, MYRCIARIA DUBIA FRUIT, ASIAN GINSENG, HYDROGEN PEROXIDE, ALPHA-ISOMETHYL IONONE, ENZYL SALICYLATE, COUMARIN, LIMONENE